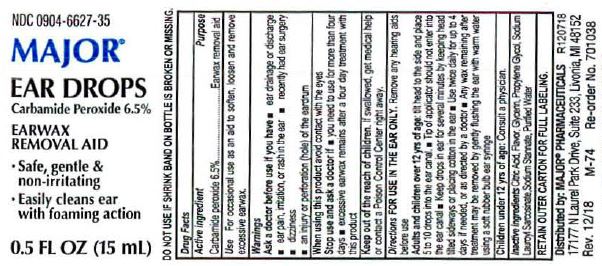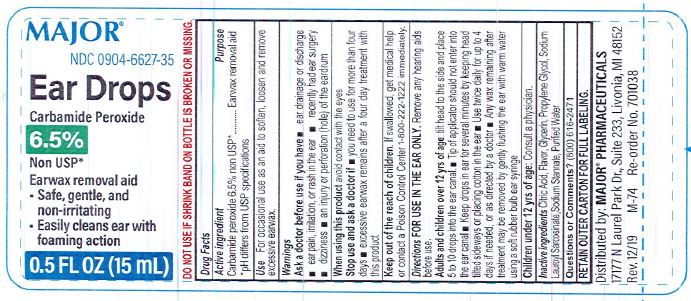 DRUG LABEL: Ear Drops
NDC: 0904-6627 | Form: LIQUID
Manufacturer: Major Pharmaceuticals
Category: otc | Type: HUMAN OTC DRUG LABEL
Date: 20250728

ACTIVE INGREDIENTS: CARBAMIDE PEROXIDE 6.5 g/100 mL
INACTIVE INGREDIENTS: SODIUM STANNATE; GLYCERIN; ANHYDROUS CITRIC ACID; PROPYLENE GLYCOL; SODIUM LAUROYL SARCOSINATE; WATER

Ear Drops Major

ACTIVE INGREDIENT

Carbamide Peroxide 6.5%

PURPOSE

Earwax Removal Aid

INDICATIONS AND USAGE

For occasional use as an aid to soften. loosen and remove excessive earwax.

Ask doctor before use if you have • ear drainage or discharge • ear pain • irritation or rash in ear • dizziness • an injury or perforation (hole) of the eardrum • recently had ear surgery

When using this product avoid contact with eyes

Stop and ask doctor before use if • you need to use for more than four days • excessive earwax remains after use of this product

Stop use and ask a doctor if you need to use for more than four days • excessive earwax remains after use of this product

Keep out of reach of the children
If product is swallowed, get medical help or contact a Poison Control Center right away

DOSAGE AND ADMINISTRATION

Directions- For use in the ear only.
Adults and children over 12 years of age:
• tilt head sideways and place 5 to 10 drops into ear
• tip of applicator should not enter ear canal
• keep drops in ear for several minutes by keeping head tilted or placing cotton in the ear
• use twice daily for up to 4 days if needed, or as directed by a doctor
• any wax remaining after treatment may be removed by gently flushing the ear with warm water, using a soft rubber bulb ear syringe
Children under 12 years of age: consult a doctor.

INACTIVE INGREDIENT

Citric Acid, Flavor, Glycerin, Propylene Glycol, Sodium Lauroyl Sarcosinate, Sodium Stannate, Water

KEEP OUT OF REACH OF CHILDREN

If swallowed, get medical help or contact a Poison Control Center right away.